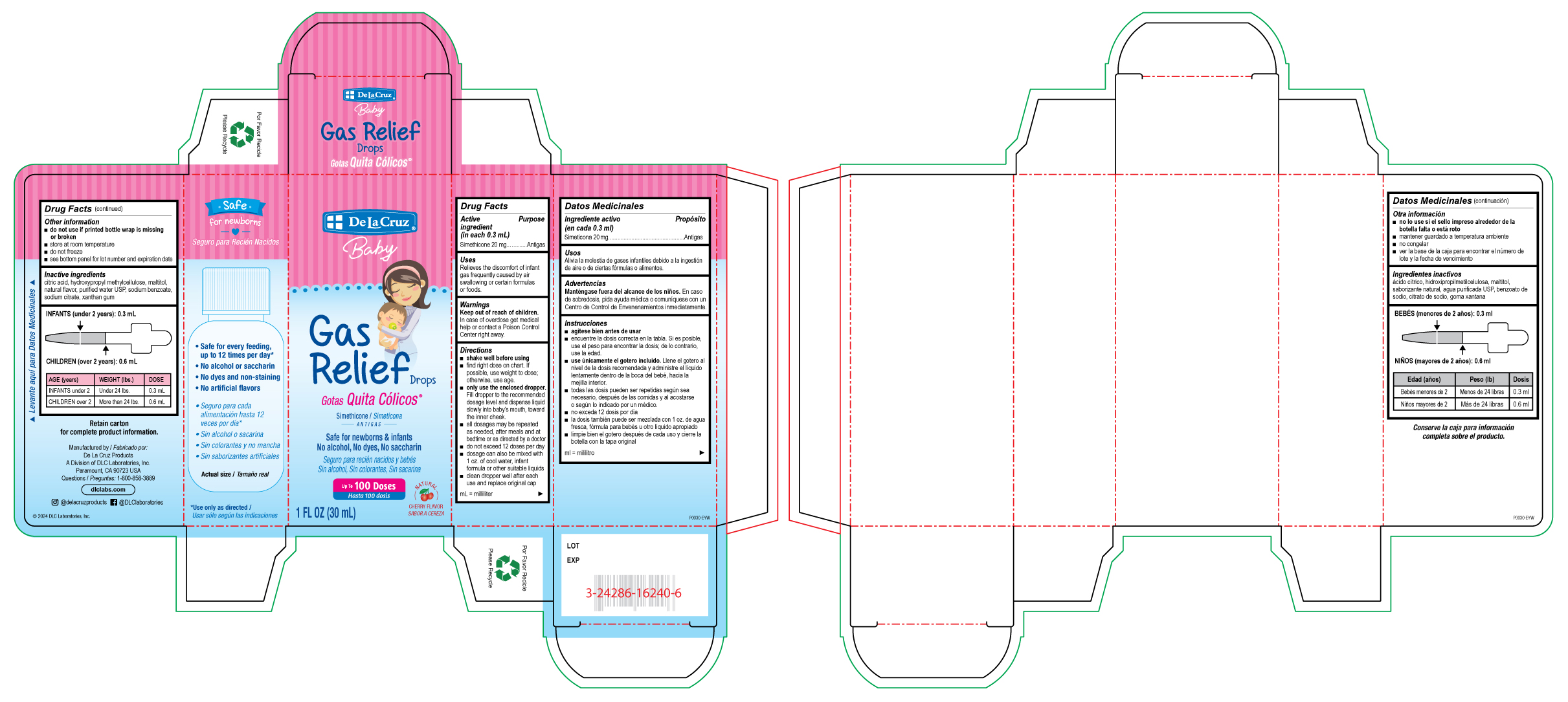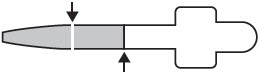 DRUG LABEL: QUITA COLICOS Gas RELIEF Drops
NDC: 24286-1533 | Form: LIQUID
Manufacturer: DLC Laboratories, Inc.
Category: otc | Type: HUMAN OTC DRUG LABEL
Date: 20260107

ACTIVE INGREDIENTS: DIMETHICONE 20 mg/0.3 mL
INACTIVE INGREDIENTS: CITRIC ACID MONOHYDRATE; HYPROMELLOSE, UNSPECIFIED; MALTITOL; WATER; SODIUM BENZOATE; SODIUM CITRATE, UNSPECIFIED FORM; XANTHAN GUM

QUITA CÓLICOS®GAS RELIEF DROPS

Drug Facts

Active ingredient (in each 0.3 mL)

Simethicone 20 mg

Purpose

Antigas

Uses

Relieves the discomfort of infant gas frequently caused by air swallowing or certain formulas or foods.

Warnings

Keep out of reach of children.In case of overdose get medical help or contact a Poison Control Center right away.

Directions

- shake well before using
- find right dose on chart. If possible, use weight to dose; otherwise, use age.
- only use the enclosed dropper.Fill dropper to the recommended dosage level and dispense liquid slowly into baby's mouth, toward the inner cheek.
- all dosages may be repeated as needed, after meals and at bedtime or as directed by a doctor
- do not exceed 12 doses per day
- dosage can also be mixed with 1 oz. of cool water, infant formula or other suitable liquids
- clean dropper well after each use and replace original cap

mL = milliliter

Other information

- do not use if printed bottle wrap is missing or broken
- store at room temperature
- do not freeze
- see bottom panel for lot number and expiration date

Inactive ingredients

citric acid, hydroxypropyl methylcellulose, maltitol, natural flavor, purified water USP, sodium benzoate, sodium citrate, xanthan gum

INFANTS (under 2 years): 0.3 mL

CHILDREN (over 2 years): 0.6 mL

AGE (years) | WEIGHT (lbs.) | DOSE
INFANTS under 2 | Under 24 lbs. | 0.3 mL
CHILDREN over 2 | More than 24 lbs. | 0.6 mL

Questions

1-800-858-3889

Manufactured by :
De La Cruz Products
A Division of DLC Laboratories, Inc.
Paramount, CA 90723 USA

PRINCIPAL DISPLAY PANEL - 30 mL Bottle Box

De La Cruz®
Baby

Gas
Relief Drops

Gotas Quita Cólicos®

Simethicone
— ANTIGAS —

Safe for newborns & infants
No alcohol, No dyes, No saccharin

Up To 100 Doses

NATURAL
CHERRY FLAVOR

1 FL OZ (30 mL)